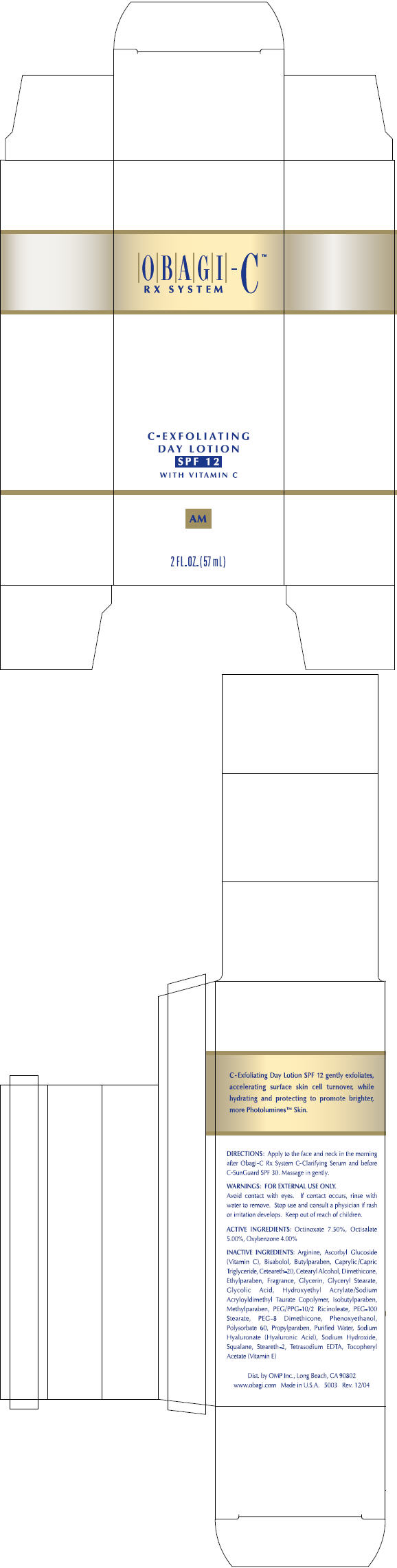 DRUG LABEL: OBAGI-C RX SYSTEM C-EXFOLIATING DAY
NDC: 62032-108 | Form: LOTION
Manufacturer: OMP, INC.
Category: otc | Type: HUMAN OTC DRUG LABEL
Date: 20120102

ACTIVE INGREDIENTS: OCTISALATE 50 mg/1 mL; OCTINOXATE 75 mg/1 mL; OXYBENZONE 40 mg/1 mL
INACTIVE INGREDIENTS: ISOBUTYLPARABEN; STEARETH-2; ASCORBYL GLUCOSIDE; LEVOMENOL; GLYCERIN; EDETATE DISODIUM; ALPHA-TOCOPHEROL ACETATE; DIMETHICONE; ARGININE; WATER; METHYLPARABEN; PROPYLPARABEN; GLYCOLIC ACID; SQUALANE; MEDIUM-CHAIN TRIGLYCERIDES; GLYCERYL MONOSTEARATE; PEG-100 STEARATE; CETOSTEARYL ALCOHOL; POLYOXYL 20 CETOSTEARYL ETHER; HYALURONATE SODIUM; SODIUM HYDROXIDE; PHENOXYETHANOL; ETHYLPARABEN; BUTYLPARABEN; POLYSORBATE 60; PEG-8 DIMETHICONE; PEG-8 RICINOLEATE

OBAGI-C™
RX SYSTEM
C-EXFOLIATING
DAY LOTION
SPF 12

DIRECTIONS

Apply to the face and neck in the morning after Obagi-C Rx System C-Clarifying Serum and before C-SunGuard SPF 30. Massage in gently.

WARNINGS

FOR EXTERNAL USE ONLY.

WHEN USING

Avoid contact with eyes. If contact occurs, rinse with water to remove.

Stop use and consult a physician if rash or irritation develops.

Keep out of reach of children.

ACTIVE INGREDIENTS

Octinoxate 7.50%, Octisalate 5.00%, Oxybenzone 4.00%

INACTIVE INGREDIENTS

Arginine, Ascorbyl Glucoside (Vitamin C), Bisabolol, Butylparaben, Caprylic/Capric Triglyceride, Ceteareth-20, Cetearyl Alcohol, Dimethicone, Ethylparaben, Fragrance, Glycerin, Glyceryl Stearate, Glycolic Acid, Hydroxyethyl Acrylate/Sodium Acryloyldimethyl Taurate Copolymer, Isobutylparaben, Methylparaben, PEG/PPG-10/2 Ricinoleate, PEG-100 Stearate, PEG-8 Dimethicone, Phenoxyethanol, Polysorbate 60, Propylparaben, Purified Water, Sodium Hyaluronate (Hyaluronic Acid), Sodium Hydroxide, Squalane, Steareth-2, Tetrasodium EDTA, Tocopheryl Acetate (Vitamin E)

Dist. by OMP Inc., Long Beach, CA 90802

PRINCIPAL DISPLAY PANEL - 57 mL Carton

OBAGI-C™
RX SYSTEM

C-EXFOLIATING
DAY LOTION
SPF 12
WITH VITAMIN C

AM

2 FL. OZ. (57 mL)